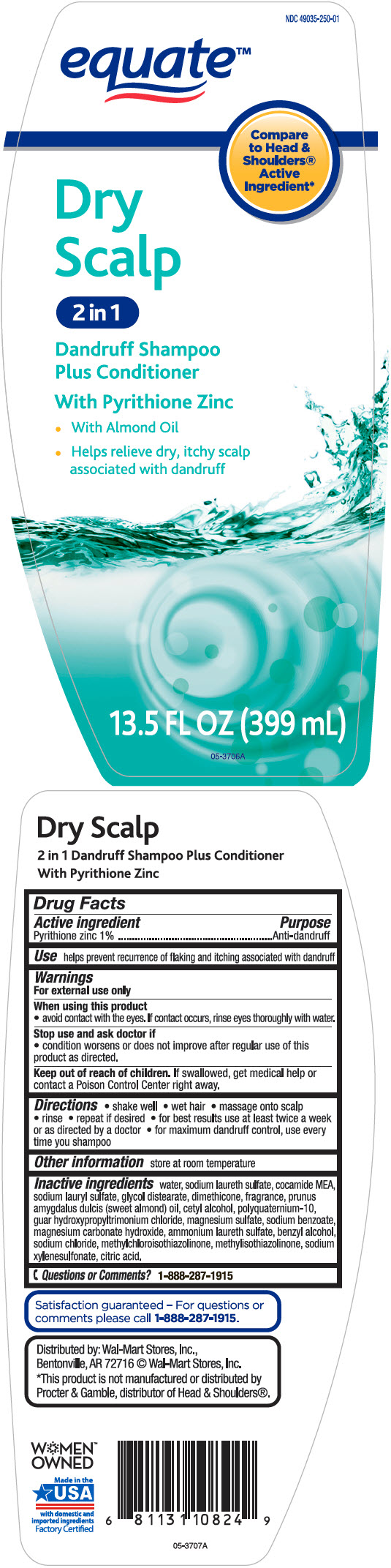 DRUG LABEL: Equate Dry Scalp 2 in 1 Dandruff SH and COND
NDC: 49035-250 | Form: SHAMPOO
Manufacturer: Wal-Mart Stores, Inc.
Category: otc | Type: HUMAN OTC DRUG LABEL
Date: 20231215

ACTIVE INGREDIENTS: Pyrithione Zinc 10 mg/1 mL
INACTIVE INGREDIENTS: Water; Sodium Laureth-3 Sulfate; Coco Monoethanolamide; Sodium Lauryl Sulfate; Glycol Distearate; Dimethicone; Almond Oil; Cetyl Alcohol; Polyquaternium-10 (30000 mpa.s at 2%); Guar Hydroxypropyltrimonium Chloride (1.7 Substituents Per Saccharide); Magnesium Sulfate, Unspecified Form; Sodium Benzoate; Magnesium Carbonate Hydroxide; Ammonium Laureth-5 Sulfate; Benzyl Alcohol; Sodium Chloride; Methylchloroisothiazolinone; Methylisothiazolinone; Sodium Xylenesulfonate; Citric Acid Monohydrate

Equate™ Dry Scalp 2 in 1 Dandruff SH & COND
Anti-Dandruff

Drug Facts

Active ingredient

Pyrithione Zinc 1%

Purpose

Anti-dandruff

Use

helps prevent recurrence of flaking and itching associated with dandruff.

Warnings

For external use only

When using this product

- avoid contact with the eyes. If contact occurs, rinse eyes thoroughly with water.

Stop use and ask a doctor if

- condition worsens or does not improve after regular use of this product as directed

Keep out of reach of children. If swallowed, get medical help or contact a Poison Control Center right away

Directions

- shake well
- wet hair
- massage onto scalp
- rinse
- repeat if desired
- for best results use at least twice a week or as directed by a doctor
- for maximum dandruff control, use every time you shampoo

Other information

store at room temperature

Inactive ingredients

water, sodium laureth sulfate, cocamide MEA, sodium lauryl sulfate, glycol distearate, dimethicone, fragrance, prunus amygdalus dulcis (sweet almond) oil, cetyl alcohol, polyquaternium-10, guar hydroxypropyltrimonium chloride, magnesium sulfate, sodium benzoate, magnesium carbonate hydroxide, ammonium laureth sulfate, benzyl alcohol, sodium chloride, methylchloroisothiazolinone, methylisothiazolinone, sodium xylenesulfonate, citric acid

Questions or Comments?

1-888-287-1915

Distributed by: Wal-Mart Stores, Inc.,
Bentonville, AR 72716

PRINCIPAL DISPLAY PANEL - 399 mL Bottle Label

NDC 49035-250-01

equate™

Compare
to Head &
Shoulders®
Active
Ingredient*

Dry
Scalp

2 in 1

Dandruff Shampoo
Plus Conditioner

With Pyrithione Zinc

- With Almond Oil
- Helps relieve dry, itchy scalp
  associated with dandruff

13.5 FL OZ (399 mL)

05-3706A